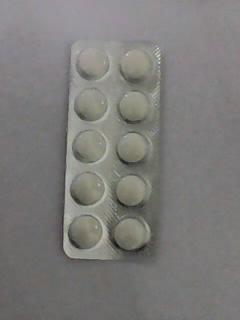 DRUG LABEL: APTRIZINE
NDC: 46084-012 | Form: TABLET
Manufacturer: A P J Laboratories Limited
Category: otc | Type: HUMAN OTC DRUG LABEL
Date: 20130221

ACTIVE INGREDIENTS: CETIRIZINE HYDROCHLORIDE 10 mg/1 1
INACTIVE INGREDIENTS: LACTOSE MONOHYDRATE 21.66 mg/1 1; STARCH, CORN 85.32 mg/1 1; GELATIN 2.4 mg/1 1; METHYLPARABEN .2 mg/1 1; TITANIUM DIOXIDE .1 mg/1 1; MAGNESIUM STEARATE 1.3 mg/1 1; TALC 3.9 mg/1 1; SODIUM STARCH GLYCOLATE TYPE A POTATO 3.9 mg/1 1

active ingredient

CETIRIZINE HYDROCHLORIDE

Purpose

Antihistamine

Keep out of reach of children.In case of overdose, get medical help or contact a Poison Control Center right away.

Indications and Usage

Temporarily relieves these symptoms due to hay fever or other upper respiratory allergies, runny nose, sneezing, itchy, watery eyes, itching of the nose or throat.

Warning

If you have ever had an allergic reaction to this product or any of its ingredients or to an antihistamine containing hydroxyzine.

Dosage and Administration

Adults and children 6years andover One 10 mg tablet once daily; do not take more than one 10 mg tablet in 24 hours.
A 5 mg product may be appropriate for less severe symptoms.
Adults 65years and over: ask a doctor.
Children under 4-6 years of age: ask a doctor
Children under 4 years of age: ask a doctor
Consumers with liver or kidney disease: ask a doctor

Inactive Ingredient

LACTOSE MONOHYDRATE

Inactive Ingredient

STARCH, CORN

Inactive Ingredient

GELATIN

Inactive Ingredient

METHYLPARABEN

Inactive Ingredient

TITANIUM DIOXIDE

Inactive Ingredient

MAGNESIUM STEARATE

Inactive Ingredient

TALC

Inactive Ingredient

SODIUM STARCH GLYCOLATE TYPE A POTATO